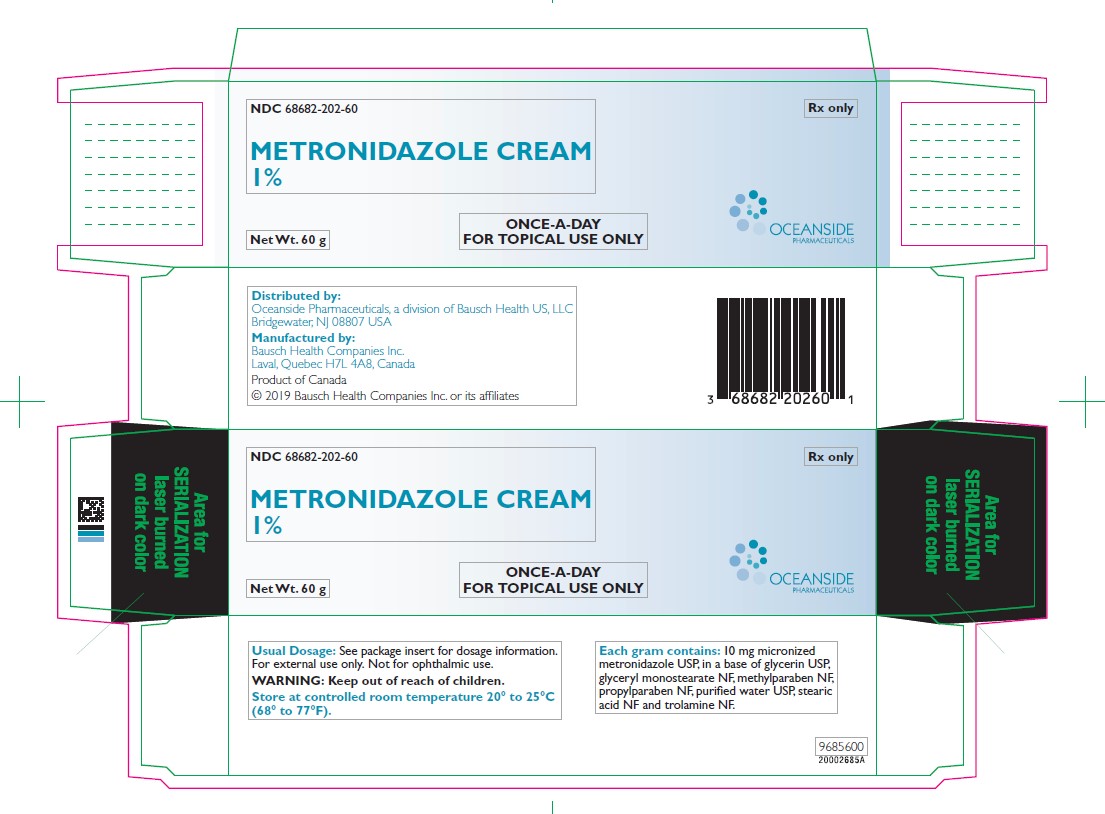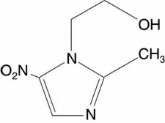 DRUG LABEL: Metronidazole
NDC: 68682-202 | Form: CREAM
Manufacturer: Oceanside Pharmaceuticals
Category: prescription | Type: HUMAN PRESCRIPTION DRUG LABEL
Date: 20220621

ACTIVE INGREDIENTS: metronidazole 10 mg/60 g
INACTIVE INGREDIENTS: water; stearic acid; glyceryl monostearate; glycerin; methylparaben; trolamine; propylparaben

METRONIDAZOLE CREAM
1%

FOR TOPICAL USE ONLY
NOT FOR OPHTHALMIC USE

DESCRIPTION

METRONIDAZOLE CREAM, 1%, contains metronidazole USP. Chemically, metronidazole is 2-methyl-5-nitro-1H-imidazole-1-ethanol. The molecular formula for metronidazole is C6H9N3O3. It has the following structural formula:

Metronidazole has a molecular weight of 171.16. It is a white to pale yellow crystalline powder. It is slightly soluble in alcohol and has a solubility in water of 10 mg/mL at 20°C. Metronidazole is a member of the imidazole class of antibacterial agents and is classified as an antiprotozoal and antibacterial agent.

METRONIDAZOLE CREAM is an emollient cream; each gram contains 10 mg micronized metronidazole USP, in a base of glycerin USP, glyceryl monostearate NF, methylparaben NF, propylparaben NF, purified water USP, stearic acid NF and trolamine NF.

CLINICAL PHARMACOLOGY

Pharmacokinetics:

When a one gram dose of METRONIDAZOLE CREAM, 1%, was applied in a single application to the face of 16 healthy volunteers, low concentrations of metronidazole were detected in the plasma of 7 of the volunteers. The mean±SD Cmax of metronidazole was 27.6±7.3 ng/mL, which is about 1% of the value reported for a single 250 mg oral dose of metronidazole. The time to maximum plasma concentration (Tmax) in the volunteers with detectable metronidazole was 8-12 hours after topical application.

Pharmacodynamics:

The mechanisms by which metronidazole acts in reducing inflammatory lesions of rosacea are unknown.

Clinical Studies:

Safety and efficacy of METRONIDAZOLE CREAM were evaluated in two randomized vehicle-controlled clinical studies for the treatment of rosacea, which excluded patients who had nodules, moderate or severe rhinophyma, dense telangiectases, plaque-like facial edema or ocular involvement and those who had a history of not responding to metronidazole therapy for rosacea. Of the patients included in the efficacy database (n=416), there were 142 men and 274 women. Endpoint efficacy data comparisons for patients treated with daily METRONIDAZOLE CREAM or vehicle applications are listed below.

Inflammatory Lesion Counts and Erythema Severity Scores in Two Clinical Trials for Rosacea
 | METRONIDAZOLE CREAM |  |  |  | Vehicle
 | Study 1 |  | Study 2 |  | Study 1 |  | Study 2
 | N | Result | N | Result | N | Result | N | Result
Papules + Pustules Count
Baseline | 89 | 15 | 92 | 19 | 50 | 18 | 49 | 17
Week 10 | 80 | 7* | 82 | 8 | 45 | 15 | 41 | 12
Reduction |  | 49%* |  | 58%* |  | 17% |  | 30%
Papules Count
Baseline | 89 | 13 | 92 | 17 | 50 | 15 | 49 | 15
Week 10 | 80 | 7* | 82 | 7 | 45 | 12 | 41 | 11
Reduction |  | 41%* |  | 55%* |  | 14% |  | 28%
Erythema Score
Baseline | 89 | 2.2 | 92 | 2.3 | 50 | 2.2 | 49 | 2.2
Week 10 | 80 | 1.3* | 82 | 1.4* | 45 | 1.7 | 40 | 1.8
Reduction |  | 42%* |  | 40%* |  | 25% |  | 19%

*Statistically significant differences between METRONIDAZOLE CREAM and vehicle groups with p≤0.05. Erythema scores: 0=none, 1=mild, 2=moderate and 3=severe.

Safety Studies:

Studies of contact sensitization (n=258), phototoxicity (n=21), and photocontact sensitization (n=29) of METRONIDAZOLE CREAM were conducted. No evidence of sensitization or phototoxicity was seen in these studies.

INDICATIONS AND USAGE

METRONIDAZOLE CREAM is indicated for the topical treatment of inflammatory lesions and erythema of rosacea.

CONTRAINDICATIONS

METRONIDAZOLE CREAM is contraindicated in those patients with a history of hypersensitivity to metronidazole or to any other ingredient in this formulation.

PRECAUTIONS

General:

If a reaction suggesting local skin irritation occurs, patients should be directed to discontinue use of the medication. Conjunctivitis associated with topical use of metronidazole on the face has been reported. Contact with the eyes should be avoided. Metronidazole is a nitroimidazole and should be used with care in patients with evidence of, or history of, blood dyscrasia.

Information for Patients:

Patients using METRONIDAZOLE CREAM should receive the following information and instructions:

1. This medication is to be used as directed.
2. It is for external use only.
3. Avoid contact with the eyes.
4. Cleanse affected area(s) before applying METRONIDAZOLE CREAM.
5. This medication should not be used for any disorder other than that for which it is prescribed.
6. Patients should report any adverse reaction to their physician.

Drug Interactions:

Oral metronidazole has been reported to potentiate the anticoagulant effect of coumarin and warfarin resulting in a prolongation of prothrombin time. Drug interactions should be kept in mind when METRONIDAZOLE CREAM is prescribed for patients who are receiving anticoagulant treatment, although they are less likely to occur with topical metronidazole administration because of low absorption. (See CLINICAL PHARMACOLOGY, Pharmacokinetics.)

Carcinogenesis, Mutagenesis, Impairment of Fertility:

Metronidazole has shown evidence of carcinogenic activity in a number of studies involving chronic, oral administration in mice and rats but not in studies involving hamsters.

In several long-term studies in mice, oral doses of approximately 225 mg/m^2/day or greater (approximately 37 times the human topical dose on a mg/m^2 basis) were associated with an increase in pulmonary tumors and lymphomas. Several long-term oral studies in the rat have shown statistically significant increases in mammary and hepatic tumors at doses >885 mg/m^2/day (144 times the topical human dose).

Metronidazole has shown evidence of mutagenic activity in several in vitro bacterial assay systems. In addition, a dose-related increase in the frequency of micronuclei was observed in mice after intraperitoneal injections. An increase in chromosomal aberrations in peripheral blood lymphocytes was reported in patients with Crohn’s disease who were treated with 200 to 1200 mg/day of metronidazole for 1 to 24 months. However, in another study, no increase in chromosomal aberrations in circulating lymphocytes was observed in patients with Crohn’s disease treated with the drug for 8 months.

In one published study, using albino hairless mice, intraperitoneal administration of metronidazole at a dose of 45 mg/m^2/day (approximately 7 times the human topical dose on a mg/m^2 basis) was associated with an increase in ultraviolet radiation-induced skin carcinogenesis. Neither dermal carcinogenicity nor photocarcinogenicity studies have been performed with METRONIDAZOLE CREAM or any marketed metronidazole formulations.

Pregnancy:

Teratogenic Effects:

There are no adequate and well-controlled studies with the use of METRONIDAZOLE CREAM in pregnant women. Metronidazole crosses the placental barrier and enters the fetal circulation rapidly. No fetotoxicity was observed after oral administration of metronidazole to rats or mice at 200 and 20 times, respectively, the expected clinical dose. However, oral metronidazole has shown carcinogenic activity in rodents. Because animal reproduction studies are not always predictive of human response, METRONIDAZOLE CREAM should be used during pregnancy only if clearly needed.

Nursing Mothers:

After oral administration, metronidazole is secreted in breast milk in concentrations similar to those found in the plasma. Even though blood levels taken after topical metronidazole application are significantly lower than those achieved after oral metronidazole, a decision should be made whether to discontinue nursing or to discontinue the drug, taking into account the importance of the drug to the mother and the risk to the infant.

Pediatric Use:

Safety and effectiveness in pediatric patients have not been established.

ADVERSE REACTIONS

Safety data from 302 patients who used METRONIDAZOLE CREAM (n=200) or vehicle control (n=102) once daily in clinical trials and experienced an adverse event considered to be treatment related include: application site reaction (METRONIDAZOLE CREAM 1, vehicle 1), condition aggravated (METRONIDAZOLE CREAM 1, vehicle 0), paresthesia (METRONIDAZOLE CREAM 0, vehicle 1), acne (METRONIDAZOLE CREAM 1, vehicle 0), dry skin (METRONIDAZOLE CREAM 0, vehicle 2). The majority of adverse reactions were mild to moderate in severity.

Two patients treated with METRONIDAZOLE CREAM once daily discontinued treatment because of adverse events: one for a severe flare of comedonal acne and one for rosacea aggravated.

Additional clinical adverse effects reported spontaneously since the drug was marketed are uncommon and include tingling or numbness of extremities, allergic reactions, skin and eye irritation, rash, headache, nausea and dry mouth.

To report SUSPECTED ADVERSE REACTIONS, contact Oceanside Pharmaceuticals at 1-800-321-4576 or FDA at 1-800-FDA-1088 or www.fda.gov/medwatch.

DOSAGE AND ADMINISTRATION

Areas to be treated should be cleansed before application of METRONIDAZOLE CREAM. Apply and rub in a thin film of METRONIDAZOLE CREAM once daily to entire affected area(s). Patients may use cosmetics after application of METRONIDAZOLE CREAM.

HOW SUPPLIED

Cream - 60 g aluminum tube - NDC 68682-202-60.

Keep out of reach of children.

Storage:

Store at controlled room temperature 20° to 25°C (68° to 77°F).

Distributed by:
Oceanside Pharmaceuticals, a division of Bausch Health US, LLC
Bridgewater, NJ 08807 USA

Manufactured by:
Bausch Health Companies Inc.
Laval, Quebec H7L 4A8, Canada

© 2019 Bausch Health Companies Inc. or its affiliates
9685700
Rev. 07/19

PRINCIPAL DISPLAY PANEL - 60 g Tube

NDC 68682-202-60

Rx only

METRONIDAZOLECREAM
1%

Net Wt. 60 g

ONCE-A-DAY
FOR TOPICAL USE ONLY
OCEANSIDE
PHARMACEUTICALS